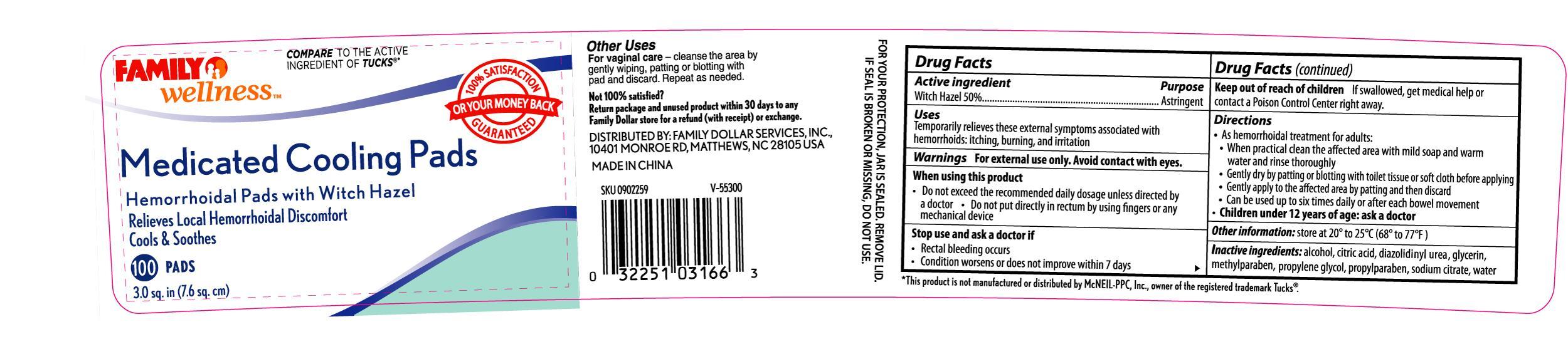 DRUG LABEL: FAMILY WELLNESS MEDICATED COOLING PADS
                
NDC: 55319-032 | Form: SOLUTION
Manufacturer: FAMILY DOLLAR
Category: otc | Type: HUMAN OTC DRUG LABEL
Date: 20120930

ACTIVE INGREDIENTS: WITCH HAZEL 5 g/1 1
INACTIVE INGREDIENTS: ALCOHOL; CITRIC ACID MONOHYDRATE; DIAZOLIDINYL UREA; GLYCERIN; METHYLPARABEN; PROPYLENE GLYCOL; PROPYLPARABEN; SODIUM CITRATE; WATER

Drug Facts

Active ingredient Purpose

Witch Hazel 50% ...............................................................Astringent

Uses

Temporarily relieves these external symptoms associated with hemorrhoids: itching, burning, and irritation

Warnings

For external use only. Avoid contact with eyes.

When using this product

- Do not exceed the recommended daily dosage unless directed by a doctor
- Do not put directly in rectum by using fingers or any mechanical device

Stop use and ask a doctor if

- Rectal bleeding occurs
- Condition worsens or does not improve within 7 days

Keep out of reach of children

If swallowed, get medical help or contact a Poison Control Center right away.

Directions

- As hemorrhoidal treatment for adults:
- When practical clean the affected area with mild soap and warm water and rinse thoroughly
- Gently dry by patting or blotting with toilet tissue or soft cloth before applying
- Gently apply to the affected area by patting and then discard
- Can be used up to six times daily or after each bowel movement
- Children under 12 years of age: ask a doctor

Other information

Store at 20o to 25oC (68o to 77oF)

INACTIVE INGREDIENT

Inactive ingredients: alcohol, citric acid, diazolidinyl urea, glycerin, methylparaben, propylene glycol, propylparaben, sodium citrate, water

DOSAGE AND ADMINISTRATION

DISTRIBUTED BY: FAMILY DOLLAR SERVICES, INC.

10401 MONROE RD, MATTHEWS, NC 28105 USA

MADE IN CHINA